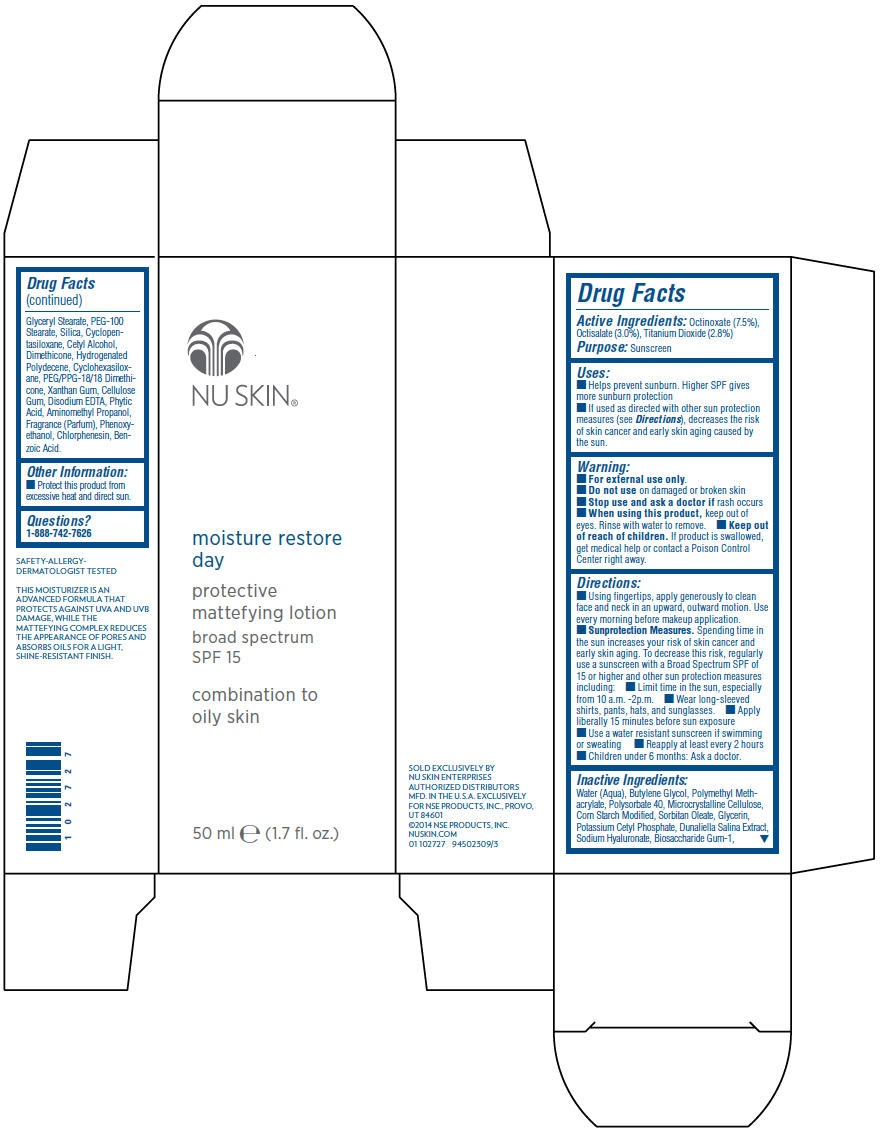 DRUG LABEL: Moisture Restore Day Protective Mattefying Broad Spectrum SPF15 Combination to Oily
NDC: 62839-0272 | Form: LOTION
Manufacturer: NSE Products, Inc.
Category: otc | Type: HUMAN OTC DRUG LABEL
Date: 20220113

ACTIVE INGREDIENTS: Octinoxate 75 mg/1 mL; Octisalate 30 mg/1 mL; Titanium Dioxide 28 mg/1 mL
INACTIVE INGREDIENTS: Water; Butylene Glycol; Polysorbate 40; Microcrystalline Cellulose; Glycerin; Sorbitan Monooleate; Potassium Cetyl Phosphate; Dunaliella Salina; Hyaluronate Sodium; Biosaccharide Gum-1; Glyceryl Monostearate; PEG-100 Stearate; Silicon Dioxide; Cyclomethicone 5; Cetyl Alcohol; Dimethicone; HYDROGENATED POLYDECENE TYPE I; Cyclomethicone 6; Xanthan Gum; Carboxymethylcellulose Sodium, Unspecified; Edetate Disodium; Fytic Acid; Aminomethylpropanol; Phenoxyethanol; Chlorphenesin; Benzoic Acid; Methylparaben; Propylparaben

Moisture Restore Day Protective Mattefying Lotion Broad Spectrum SPF15 Combination to Oily

Drug Facts

Active Ingredients

Octinoxate (7.5%), Octisalate (3.0%), Titanium Dioxide (2.8%)

Purpose

Sunscreen

Uses

- Helps prevent sunburn. Higher SPF gives more sunburn protection
- If used as directed with other sun protection measures (see Directions), decreases the risk of skin cancer and early skin aging caused by the sun.

Warning

- For external use only.

- Do not use on damaged or broken skin

- Stop use and ask a doctor if rash occurs

- When using this product, keep out of eyes. Rinse with water to remove.

- Keep out of reach of children. If product is swallowed, get medical help or contact a Poison Control Center right away.

Directions

- Using fingertips, apply generously to clean face and neck in an upward, outward motion. Use every morning before makeup application.
- Sunprotection Measures. Spending time in the sun increases your risk of skin cancer and early skin aging. To decrease this risk, regularly use a sunscreen with a Broad Spectrum SPF of 15 or higher and other sun protection measures including:
  - Limit time in the sun, especially from 10 a.m. -2p.m.
  - Wear long-sleeved shirts, pants, hats, and sunglasses.
  - Apply liberally 15 minutes before sun exposure
  - Use a water resistant sunscreen if swimming or sweating
  - Reapply at least every 2 hours
  - Children under 6 months: Ask a doctor.

Inactive Ingredients

Water (Aqua), Butylene Glycol, Polymethyl Methacrylate, Polysorbate 40, Microcrystalline Cellulose, Corn Starch Modified, Sorbitan Oleate, Glycerin, Potassium Cetyl Phosphate, Dunaliella Salina Extract, Sodium Hyaluronate, Biosaccharide Gum-1, Glyceryl Stearate, PEG-100 Stearate, Silica, Cyclopentasiloxane, Cetyl Alcohol, Dimethicone, Hydrogenated Polydecene, Cyclohexasiloxane, PEG/PPG-18/18 Dimethicone, Xanthan Gum, Cellulose Gum, Disodium EDTA, Phytic Acid, Aminomethyl Propanol, Fragrance (Parfum), Phenoxyethanol, Chlorphenesin, Benzoic Acid.

Other Information

- Protect this product from excessive heat and direct sun.

Questions?

1-888-742-7626

PRINCIPAL DISPLAY PANEL - 50 ml Bottle Carton

NU SKIN®

moisture restore
day

protective
mattefying lotion
broad spectrum
SPF 15

combination to
oily skin

50 ml e (1.7 fl. oz.)